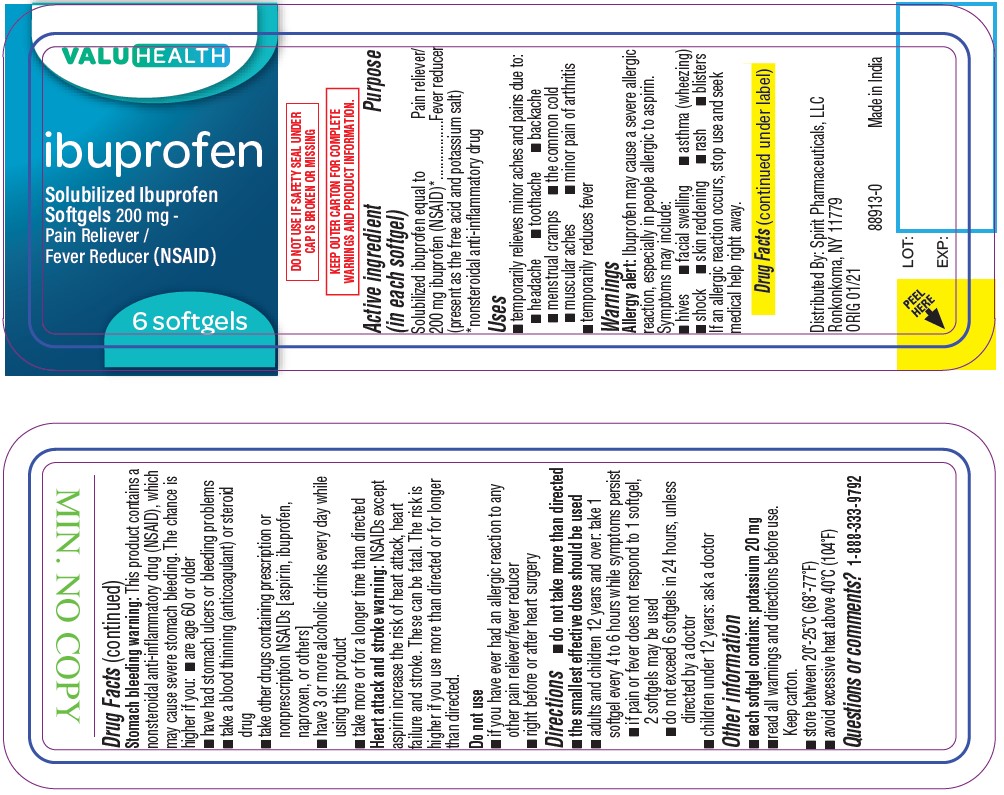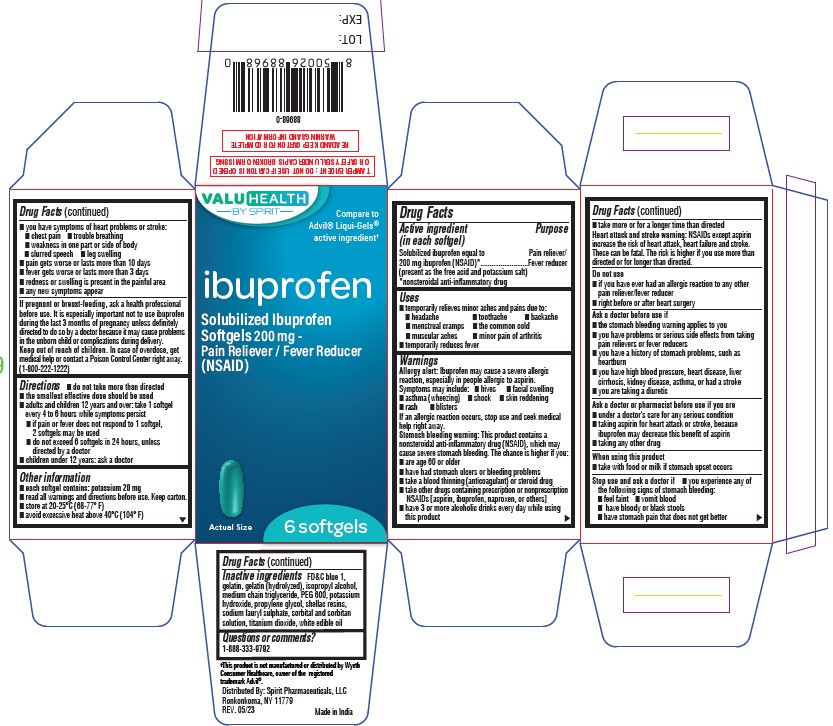 DRUG LABEL: IBUPROFEN
NDC: 68210-4205 | Form: CAPSULE, LIQUID FILLED
Manufacturer: SPIRIT PHARMACEUTICALS,LLC
Category: otc | Type: HUMAN OTC DRUG LABEL
Date: 20241230

ACTIVE INGREDIENTS: IBUPROFEN 200 mg/1 1
INACTIVE INGREDIENTS: TITANIUM DIOXIDE; SORBITAN; GELATIN; FD&C BLUE NO. 1; GELATIN HYDROLYZATE (PORCINE SKIN, MW 3000); ISOPROPYL ALCOHOL; MEDIUM-CHAIN TRIGLYCERIDES; POLYETHYLENE GLYCOL 600; POTASSIUM HYDROXIDE; PROPYLENE GLYCOL; SHELLAC; SODIUM LAURYL SULFATE

IBUPROFEN SOFTGEL

Drug Facts

Active ingredients (in each Capsule)

Solubilized ibuprofen equal to 200 mg ibuprofen (NSAID)*

Purpose

Pain reliever /fever reducer

Uses

- Temporarily relieves minor aches and pains due to :
  - headache
  - toothache
  - backache
  - menstrual cramps
  - the common cold
  - muscular aches
  - minor pain of arthritis
- temporarily reduces fever

Warnings

Allergy alert

Ibuprofen may cause a severe allergic reaction, especially in people allergic to aspirin. Symptoms may include:

- hives
- facial swelling
- asthma (wheezing)
- shock
- skin reddening
- rash
- blisters

If an allergic reaction occurs, stop use and seek medical help right away.

Stomach bleeding warning

This product contains a nonsteroidal anti-inflammatory drug (NSAID), which may cause severe stomach bleeding. The chance is higher if you:

- are age 60 or older
- have had stomach ulcers or bleeding problems
- take a blood thinning (anticoagulant) or steroid drug
- take other drugs containing prescription or nonprescription NSAIDs [aspirin, ibuprofen, naproxen, or others]
- have 3 or more alcoholic drinks every day while using this product
- take more or for a longer time than directed

Heart attack and stroke warning

NSAID's except aspirin increases the risk of heart attack, heart failure and stroke. These can be fatal. The risk is higher if you use more than directed or longer than directed.

Do not use

- if you have ever had an allergic reaction to any other pain reliever / fever reducer
- right before or after heart surgery

Ask a doctor before use if

- the stomach bleeding warning applies to you
- you have problems or serious side effects from taking pain relievers or fever reducers
- you have stomach problems, such as heartburn
- you have high blood pressure, heart disease, liver cirrhosis, kidney disease or asthma
- you are taking a diuretic

Ask a doctor or pharmacist before use if you are

- under a doctor's care for any serious condition
- taking aspirin for heart attack or stroke, because ibuprofen may decrease this benefit of aspirin
- taking any other drug

When using this product

- take with food or milk if stomach upset occurs
- the risk of heart attach or stroke may increase if you use more than directed or for longer than directed

Stop use and Ask a doctor if

- you experience any of the following signs of stomach bleeding:
  - feel faint
  - vomit blood
  - have bloody or black stools
  - have stomach pain that does not get better
- pain gets worse or lasts more than 10 days
- fever gets worse or lasts more than 3 days
- stomach pain or upset gets worse or lasts
- redness or swelling is present in the painful are
- any new symptoms appear

PREGNANCY OR BREAST FEEDING

If pregnant or breast-feeding, ask a health professional before use. It is especially important not to use ibuprofen during the last 3 months of pregnancy unless definitely directed to do so by a doctor because it may cause problems in the unborn child or complications during delivery.

Keep out of reach of children. In case of overdose, get medical help or contact a Poison Control Center right away. (1-800-222-1222)

Directions

- do not take more than directed
- the smallest effective dose should be used
- do not take longer than 10 days, unless directed by a doctor (see Warnings)
- adults ad children 12 years and over: take 1 capsule every 4 to 6 hours while symptoms persist
  - if pain or fever does not respond to 1 capsule, 2 capsules my be used
  - do not exceed 6 capsules in 24 hours, unless directed by a doctor
- children under 12 years: ask a doctor

Other information

- each capsule contains: potassium 20 mg
- read all warnings and directions before use. Keep carton.
- store between 20° - 25°C (68° - 77°F)
- avoid excessive heat above 40°C (104°F)

Inactive ingredients

FD&C blue 1, gelatin, gelatin (hydrolyzed), isopropyl alcohol, medium chain triglyceride, PEG 600, potassium hydroxide, propylene glycol, shellac resins, sodium lauryl sulphate, sorbital and sorbitan solution, titanium dioxide, white edible oil